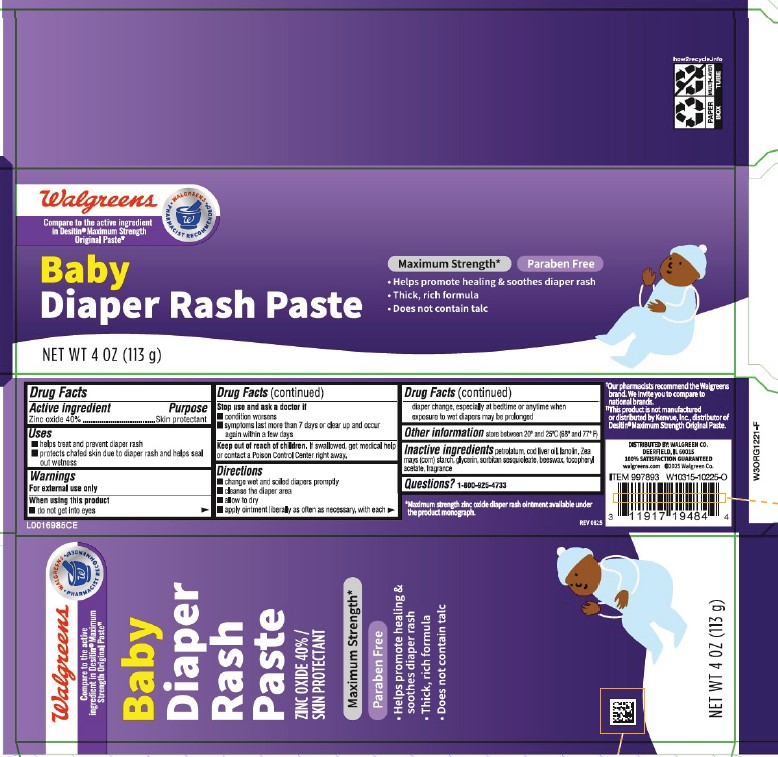 DRUG LABEL: Zinc Oxide
NDC: 0363-1020 | Form: PASTE
Manufacturer: Walgreen Co.
Category: otc | Type: HUMAN OTC DRUG LABEL
Date: 20260212

ACTIVE INGREDIENTS: ZINC OXIDE 400 mg/1 g
INACTIVE INGREDIENTS: PETROLATUM; COD LIVER OIL; LANOLIN; STARCH, CORN; GLYCERIN; SORBITAN SESQUIOLEATE; YELLOW WAX; TOCOPHEROL

Walgreen 020.002/020AC-AD
Diaper Rash Paste

Active ingredient

Zinc oxide 40%

Purpose

Skin Protectant

Uses

- helps treat and prevent diaper rash
- protects chafed skin due to the diaper rash and helps seal out wetness

Warnings

For external use only

When using this product

- do not get into eyes

Stop use and ask a doctor if

- condition worsens
- symptoms last more than 7 days or clear up and occur again within a few days

Keep out of reach of children.

If swallowed, get medical help or contact a Poison Control Center right away.

Directions

- change wet and soiled diapers promptly
- cleanse the diaper area
- allow to dry
- apply ointment liberally as often as necessary, with each diaper change, especially at bedtime or anytime when exposure to wet diapers may be prolonged

Other information

- store between 20⁰ and 25⁰C (68⁰ and 77⁰F)

Inactive ingredients

petrolatum, cod liver oil, lanolin, Zea mays (corn) starch, glycerin, sorbitan sesquioleate, beeswax, tocopheryl acetate, fragrance

Questions?

Call 1-800-925-4733

Claims/Disclaimers

*Maximum strength zinc oxide diaper rash ointment available under the product monograph.

†Our pharmacists recommend the Walgreens brand. We invite you to compare to national brands.

‡This product is not manufactured or distributed by Kenvue, Inc., distributor of Desitin® Maximum Strength Original Paste.

ADVERSE REACTION

Distributed by Walgreen Co.

Deerfield, IL 60015

100% Satisfaction Guaranteed

walgreens.com ©2025 Walgreen Co.

how2recycle.info

PAPER BOX

MULTI-LAYER TUBE

principal display panel

Walgreens

WALGREENS PHARMACIST RECOMMENDED†

Compare to the active ingredient in Desitin® Maximum Strength Original Paste‡

Baby diaper rash paste

Maximum strength*

Paraben free

- Helps promote healing & soothes diaper rash
- Thick, rich formula
- Does not contain talc

NET WT 4 OZ (113 g)